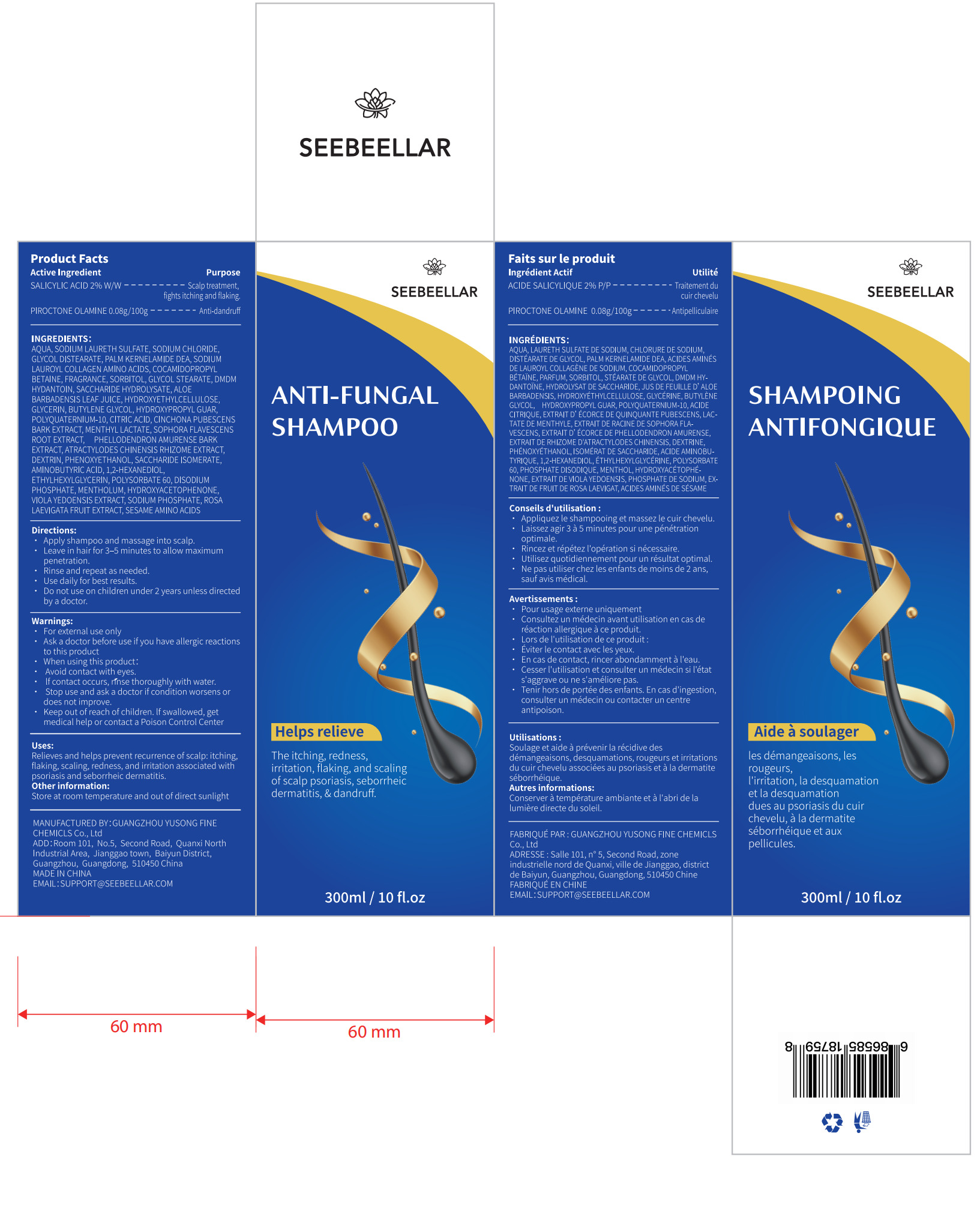 DRUG LABEL: anti-fungal
NDC: 84558-012 | Form: SHAMPOO
Manufacturer: GUANGZHOU YUSONG FINE CHEMICLS Co., Ltd
Category: otc | Type: HUMAN OTC DRUG LABEL
Date: 20250729

ACTIVE INGREDIENTS: PIROCTONE OLAMINE 0.08 g/100 mL; SALICYLIC ACID 2 g/100 mL
INACTIVE INGREDIENTS: ALOE BARBADENSIS LEAF JUICE; GUARAPROLOSE (1300 MPA.S AT 1%); CINCHONA PUBESCENS BARK; DISODIUM PHOSPHATE; SACCHARIDE ISOMERATE; AMINOBUTYRIC ACID; 1,2-HEXANEDIOL; SODIUM PHOSPHATE; GLYCOL STEARATE; PHELLODENDRON AMURENSE BARK; PHENOXYETHANOL; DMDM HYDANTOIN; BUTYLENE GLYCOL; CITRIC ACID; HYDROXYETHYLCELLULOSE; ROSA LAEVIGATA FRUIT; ETHYLHEXYLGLYCERIN; MENTHYL LACTATE; SOPHORA FLAVESCENS ROOT; MENTHOL; DEXTRIN, CORN; POLYSORBATE 60; HYDROXYACETOPHENONE; MAIZE INVERT SUGAR; AQUA; SODIUM LAURETH SULFATE; SODIUM CHLORIDE; GLYCOL DISTEARATE; COCAMIDOPROPYL BETAINE; SORBITOL; GLYCERIN; POLYQUATERNIUM-10 (1000 MPA.S AT 2%)

84558-012

Active Ingredient(s)

SALICYLIC ACID 2%

PIROCTONE OLAMINE 0.08%

Purpose

Scalp treatment
fights itching and flaking
Anti-dandruff

Use

Relieves and helps prevent recurrence of scalp: itching,
flaking, scaling, redness, and iritation associated with
psoriasis and seborrheic dermatitis.

Warnings

For external use only
Ask a doctor before use if you have allergic reactions to this product

Do not use on children under 2 years unless directed by a doctor.

When using this product:
Avoid contact with eyes.
If contact occurs, rnse thoroughly with water.

Stop use and ask a doctor if condition worsens or does not improve.

Keep out of reach of children. If swallowed, get medical help or contact a Poison Control Center

Directions

1. Apply shampoo and massage into scalp.
2. Leave in hair for 3- 5 minutes to allow maximum penetration.
3. Rinse and repeat as needed.
4. Use daily for best results.
5. Do not use on children under 2 years unless directed by a doctor.

Other information

Store at room temperature and out of direct sunlight

Inactive ingredients

AQUA, SODIUM LAURETH SULFATE, SODIUM CHLORIDE,
GLYCOL DISTEARATE, PAL .M KERNEL AMIDE DEA, SODIUM
L AUROYL COLLAGEN AMINO ACIDS, COCAMIDOPROPYL
BETAINE, FRAGRANCE, SORBITOL, GLYCOL STEARATE, DMDM
HYDANTOIN, SACCHARIDE HYDROLYSATE, ALOE
BARBADENSIS L EAF JUICE, HYDROXYETHYLCELLULOSE,
GLYCERIN, BUTYL ENE GLYCOL, HYDROXYPROPYL GUAR,
POLYQUATERNIUM-10, CITRIC ACID, CINCHONA PUBESCENS
BARK EXTRACT, MENTHYL LACTATE, SOPHORA FLAVESCENS
ROOT EXTRACT，PHEL LODENDRON AMURENSE BARK
EXTRACT, ATRACTYLODES CHINENSIS RHIZOME EXTRACT,
DEXTRIN, PHENOXYETHANOL, SACCHARIDE ISOMERATE,
AMINOBUTYRIC ACID, 1,2-HEXANEDIOL,
ETHYL HEXYL GLYCERIN, POLYSORBATE 60, DISODIUM
PHOSPHATE, MENTHOLUM, HYDROXYACETOPHENONE,
VIOL A YEDOENSIS EXTRACT, SODIUM PHOSPHATE, ROSA
L AEVIGATA FRUIT EXTRACT, SESAME AMINO ACIDS